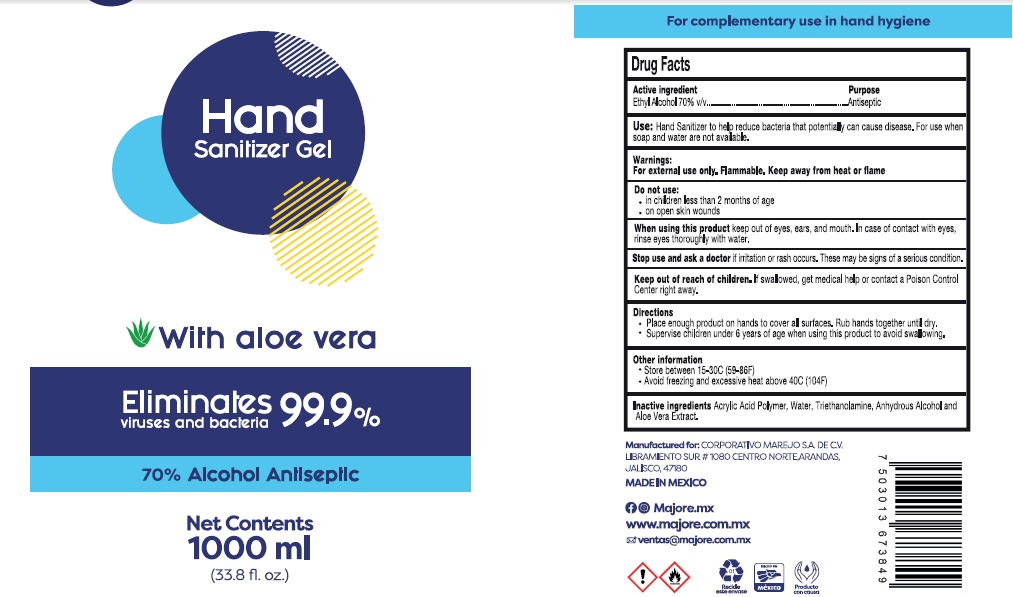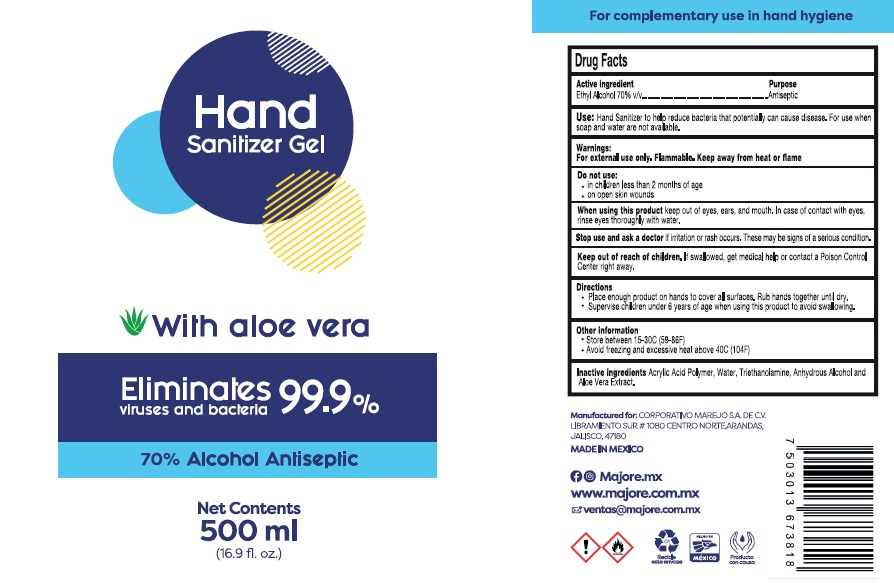 DRUG LABEL: MAREJO
NDC: 79927-1000 | Form: GEL
Manufacturer: CORPORATIVO MAREJO, S.A. DE C.V.
Category: otc | Type: HUMAN OTC DRUG LABEL
Date: 20200805

ACTIVE INGREDIENTS: ALCOHOL 0.7 mL/1 mL
INACTIVE INGREDIENTS: ALOE VERA LEAF 0.00278 mL/1 mL; TRIETHANOLAMINE CAPROYL GLUTAMATE 0.002 mL/1 mL; WATER 0.29322 mL/1 mL; ACRYLIC ACID/ETHYLENE COPOLYMER (600 MPA.S) 0.002 mL/1 mL

HAND SANITIZER GEL WITH ALOE VERA

ACTIVE INGREDIENT

Active ingredient Ethyl Alcohol 70%

PURPOSE

Purpose Antmicrobial

INDICATIONS AND USAGE

Directions

Place enough product on hands to cover all surfaces. Rub hands together until dry.

Use[s]

Hand Sanitizer to help reduce bacteria that potentially can cause disease. For use when soap and water are not available.

DOSAGE AND ADMINISTRATION

Place enough product on hands to cover all surfaces. Rub hands together until dry.

WARNINGS AND PRECAUTIONS

When using this product keep out of eyes, ears, and mouth. In case of contact with eyes, rinse eyes thoroughly with water.

Store below 110°F (43°C)

WARNINGS

For external use only. Flammable. Keep away from heat or flame

Keep out of reach of children. If swallowed, get medical help or contact a Poison Control Center right away.

STOP USE SECTION

Stop use and ask a doctor if irritation or rash occurs. These may be signs of a serious condition.

INACTIVE INGREDIENTS

ACRYLIC ACID POLYMER, WATER, TRIETHANOLAMINE, ALOE VERA